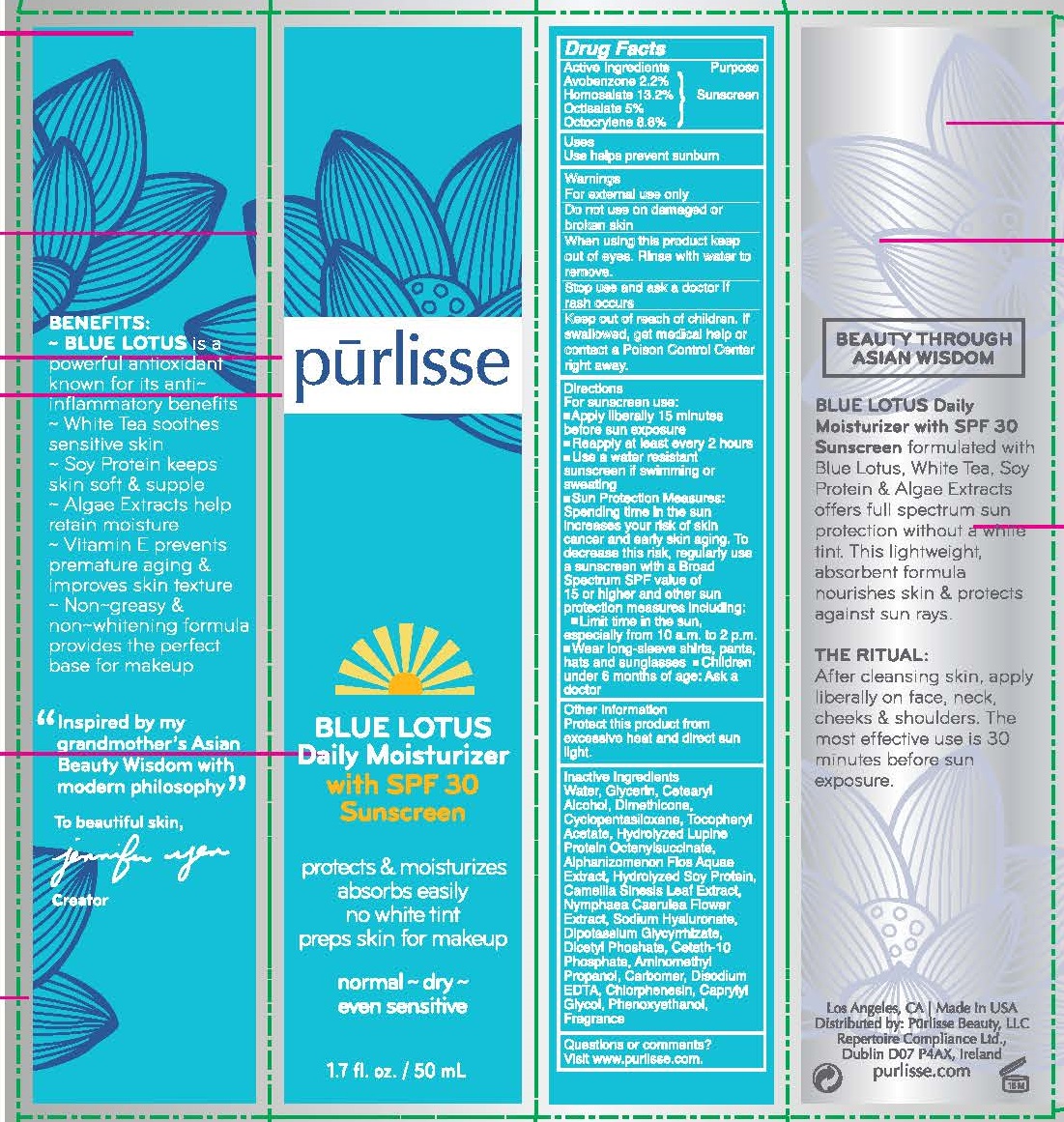 DRUG LABEL: PURLISSE BLUE LOTUS DAILY MOISTURIZER

NDC: 72407-401 | Form: LOTION
Manufacturer: Pur-Lisse Beauty, LLC
Category: otc | Type: HUMAN OTC DRUG LABEL
Date: 20220117

ACTIVE INGREDIENTS: AVOBENZONE 2.2 g/100 mL; HOMOSALATE 13.2 g/100 mL; OCTISALATE 5 g/100 mL; OCTOCRYLENE 8.8 g/100 mL
INACTIVE INGREDIENTS: WATER; GLYCERIN; CETOSTEARYL ALCOHOL; DIMETHICONE; CYCLOMETHICONE 5; .ALPHA.-TOCOPHEROL ACETATE; HYDROLYZED LUPINUS ALBUS SEED PROTEIN (ENZYMATIC; 3500 MW); APHANIZOMENON FLOSAQUAE; HYDROLYZED SOY PROTEIN (ENZYMATIC; 2000 MW); GREEN TEA LEAF; NYMPHAEA CAERULEA FLOWER; HYALURONATE SODIUM; GLYCYRRHIZINATE DIPOTASSIUM; DIHEXADECYL PHOSPHATE; CETETH-10 PHOSPHATE; AMINOMETHYLPROPANOL; CARBOMER HOMOPOLYMER, UNSPECIFIED TYPE; EDETATE DISODIUM; CHLORPHENESIN; CAPRYLYL GLYCOL; PHENOXYETHANOL

PURLISSE BLUE LOTUS DAILY MOISTURIZER WITH SPF 30 SUNSCREEN (72407-401)

ACTIVE INGREDIENTS

AVOBENZONE 2.2%

HOMOSALATE 13.2%

OCTISALATE 5%

OCTOCRYLENE 8.8%

Purpose

SUNSCREEN

Use

USE TO HELP PREVENT SUNBURN

Warnings

FOR EXTERNAL USE ONLY.

DO NOT USE ON DAMAGED OR BROKEN SKIN.

WHEN USING THIS PRODUCTKEEP OUT OF EYES. RINSE WITH WATER TO REMOVE.

STOP USE AND ASK A DOCTOR IF RASH OCCURS

Keep out of reach of children. If swallowed, get medical help or contact a Poison Control Center right away.

Directions

FOR SUNSCREEN USE:

- APPLY LIBERALLY 15 MINUTES BEFORE SUN EXPOSURE.
- REAPPLY AT LEAST EVERY 2 HOURS.
- USE A WATER RESISTANT SUNSCREEN IF SWIMMING OR SWEATING.

SUN PROTECTION MEASURES:

- SPENDING TIME IN THE SUN INCREASES YOUR RISK OF SKIN CANCER AND EARLY SKIN AGING. TO DECREASE THIS RISK, REGULARLY USE A SUNSCREEN WITH A BROAD SPECTRUM SPF VALUE OF 15 OR HIGHER AND OTHER SUN PROTECTION MEASURES INCLUDING:
- LIMIT TIME IN THE SUN, ESPECIALLY FROM 10 A.M. TO 2 P.M.
- WEAR LONG-SLEEVED SHIRTS, PANTS, HATS AND SUNGLASSES
- CHILDREN UNDER 6 MONTHS OF AGE: ASK A DOCTOR

Other information

PROTECT THIS PRODUCT FROM EXCESSIVE HEAT AND DIRECT SUN LIGHT.

Inactive ingredients

Water, Glycerin, Cetearyl Alcohol, Dimethicone, Cyclopentasiloxane, Tocopheryl Acetate, Hydrolyzed Lupine Protein Octenylsuccinate, Aphanizomenon Flos Aquae Extract, Hydrolyzed Soy Protein, Camellia Sinensis Leaf Extract, Nymphaea Coerulea Flower Extract, Sodium Hyaluronate, Dipotassium Glycyrrhizate, Dicetyl Phosphate, Ceteth-10 Phosphate, Aminomethyl Propanol, Carbomer, Disodium EDTA, Chlorphenesin, Caprylyl Glycol, Phenoxyethanol, Fragrance